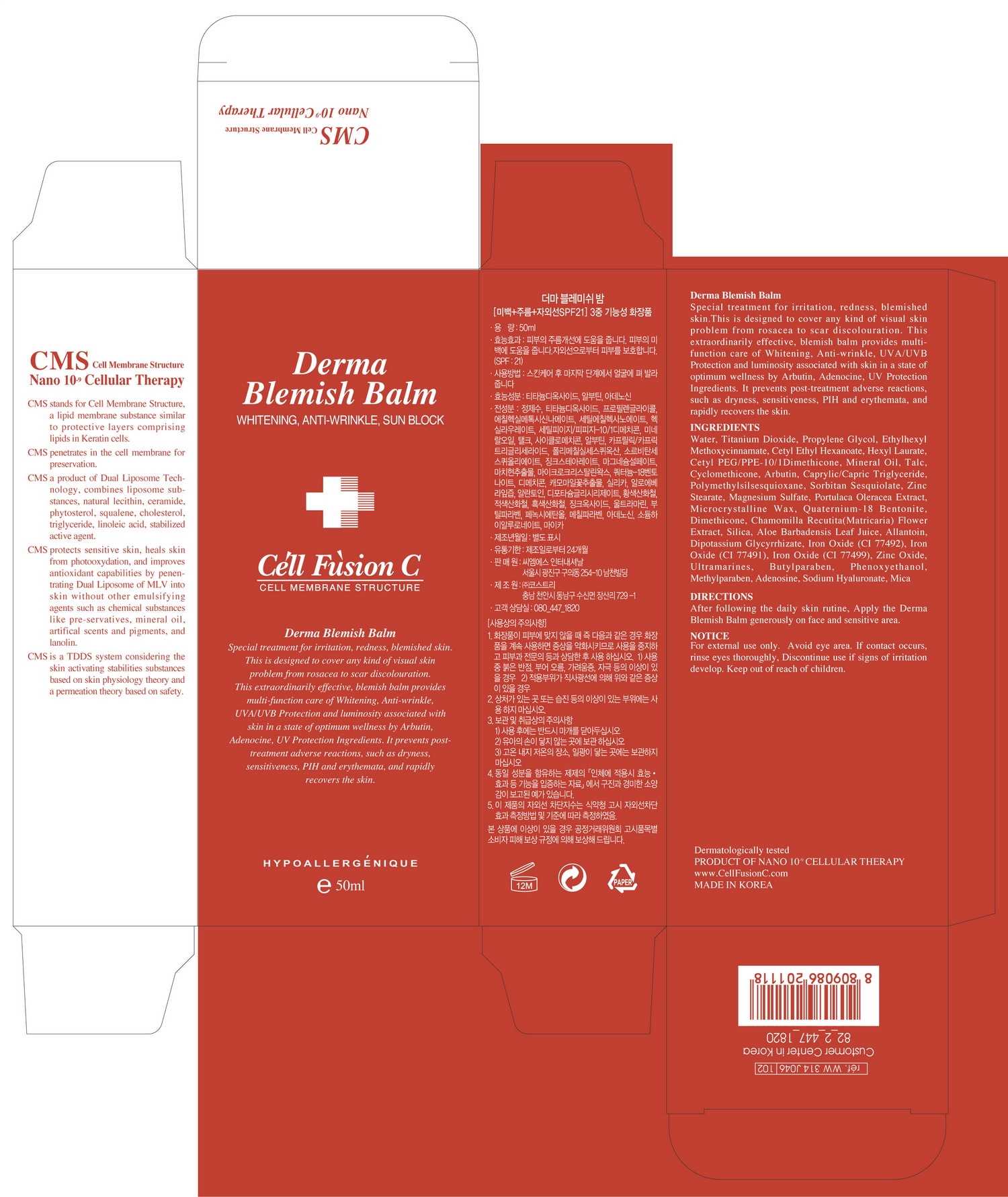 DRUG LABEL: Derma Blemish Balm
NDC: 52554-4001 | Form: CREAM
Manufacturer: Universal Cosmetic Co., Ltd
Category: otc | Type: HUMAN OTC DRUG LABEL
Date: 20100805

ACTIVE INGREDIENTS: ADENOSINE 0.0004 mL/1 mL; TITANIUM DIOXIDE 0.06 mL/1 mL; ARBUTIN 0.02 mL/1 mL

Drug Facts

Active Ingredients: Titanium dioxide, Arbutin, Adenosine

Uses
■ Helps relieve irritation, redness, blemished skin
■ Helps cover visible skin problem
■ Helps to repair aging skin including wrinkles
■ Helps prevent surnburn
■ Provides multi-function care of whitening
Warning
For external use only
When using this product
■ Avoid eye area. If contact occurs, rinse eyes thoroughly
■ If following abnormal symptoms occurs after use, stop use and ask doctor
l red specks, swelling, itching
■ Don’t use on the part where there is injury, eczema, or dermatitis
Keep out of reach of the children
Direction
■ After following the daily skin routine, Apply the Derma Blemish Balm generously on face and sensitive area as the final step.
Other Information
■ store between 20-25 °C (68-77 °F)
■ avoid freezing and excessive heat above 40 °C (104 °F)
■ close cap after use.